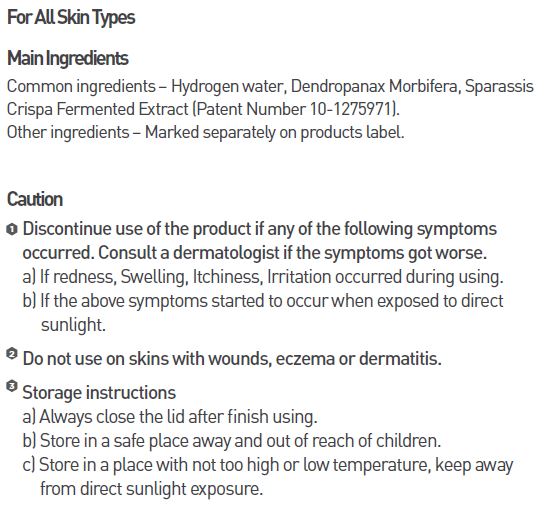 DRUG LABEL: MEDI HYDRO DP TONER
NDC: 70694-0006 | Form: LIQUID
Manufacturer: Inc MBG
Category: otc | Type: HUMAN OTC DRUG LABEL
Date: 20190124

ACTIVE INGREDIENTS: GLYCERIN 0.5 g/100 mL
INACTIVE INGREDIENTS: WATER; BUTYLENE GLYCOL

INDICATIONS AND USAGE

Apply enough amount using cotton pad or hand and allow it to absorb, every day and night after face wash

Keep out of reach of children.

DOSAGE AND ADMINISTRATION

for external use only

WARNINGS

Discontinue use of the product if any of the following symptoms occurred. Consult a dermatologist if the symptoms got worse.
a) If redness, Swelling, Itchiness, Irritation occurred during using.
b) If the above symptoms started to occur when exposed to direct sunlight.
Do not use on skins with wounds, eczema or dermatitis.

Storage instructions
a) Always close the lid after finish using.
b) Store in a safe place away and out of reach of children.
c) Store in a place with not too high or low temperature, keep awayfrom direct sunlight exposure.

PURPOSE

Covers and protects sensitive skin with its fresh and moisturizing effects.

INACTIVE INGREDIENT

water, butylene glycol, niacinamide, hyaluronic acid, etc.

ACTIVE INGREDIENT

glycerin